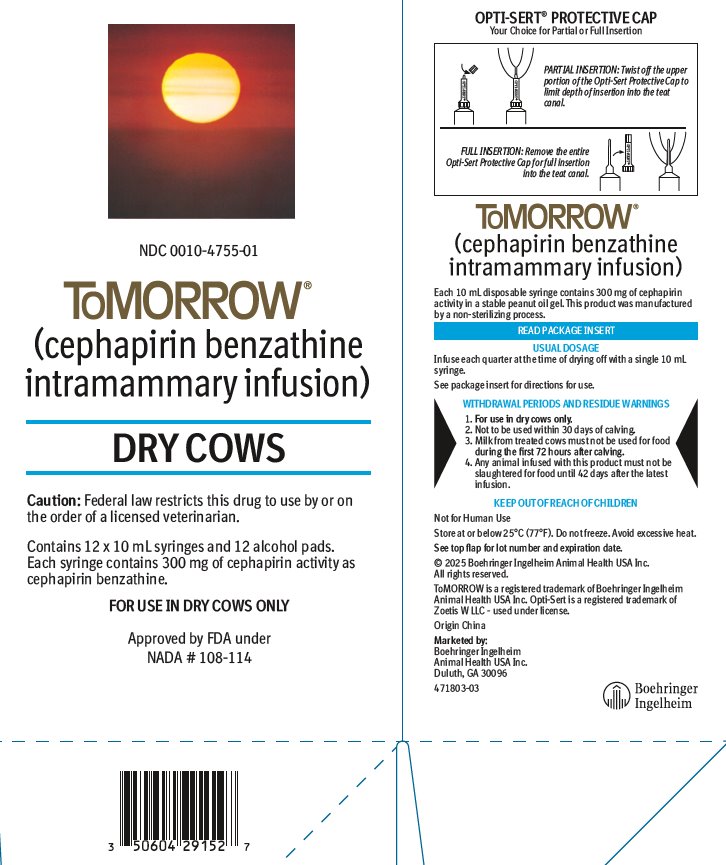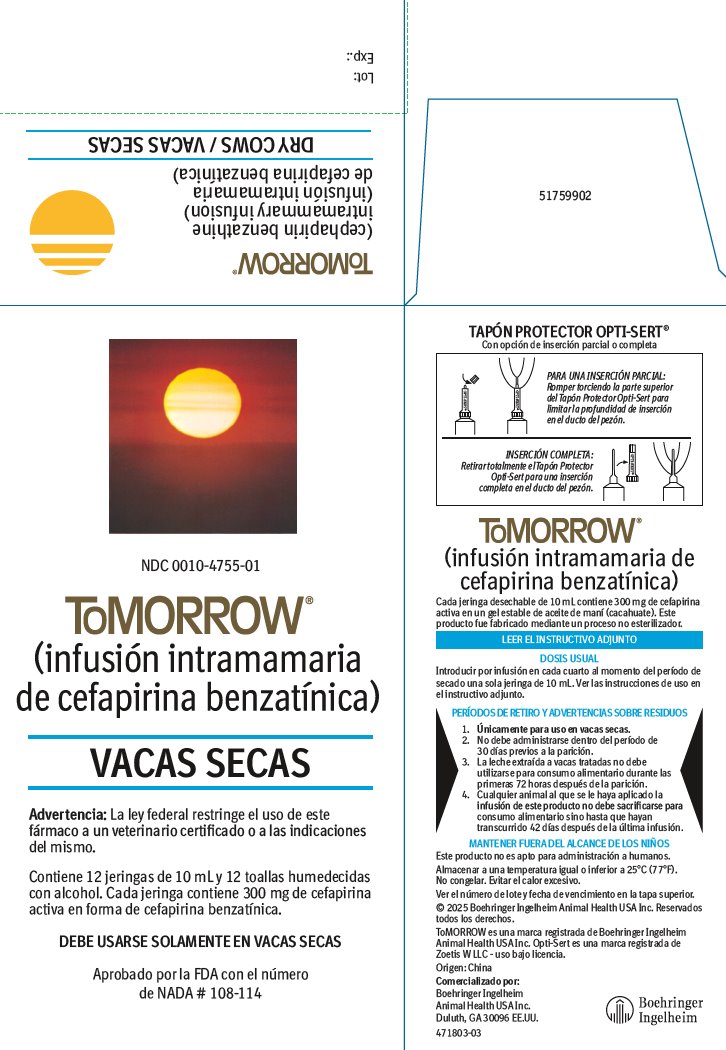 DRUG LABEL: ToMORROW
NDC: 0010-4755 | Form: SUSPENSION
Manufacturer: Boehringer Ingelheim Animal Health USA Inc.
Category: animal | Type: PRESCRIPTION ANIMAL DRUG LABEL
Date: 20251223

ACTIVE INGREDIENTS: CEPHAPIRIN BENZATHINE 300 mg/10 mL

ToMORROW®
(cephapirin benzathine intramammary infusion)
(infusión intramamaria de cefapirina benzatínica)

FOR USE IN DRY COWS ONLY
DEBE USARSE SOLAMENTE EN VACAS SECAS

Approved by FDA under NADA # 108-114

Aprobado por la FDA con el número de NADA # 108-114

Caution: Federal law restricts this drug to use by or on the order of a licensed veterinarian.

Advertencia: La ley federal restringe el uso de este fármaco a un veterinario certificado o a las indicaciones del mismo.

DESCRIPTION

ToMORROW (cephapirin benzathine intramammary infusion) is a product which provides a wide range of bactericidal activity against gram-positive and gram-negative organisms. It is derived biosynthetically from 7-aminocephalosporanic acid.

Each 10 mL disposable syringe contains 300 mg of cephapirin activity in a stable peanut oil gel. This product was manufactured by a non-sterilizing process.

DESCRIPCIÓN

ToMORROW (infusión intramamaria de cefapirina benzatínica) es un producto que proporciona un amplio espectro de actividad bactericida contra organismos grampositivos y gramnegativos. El producto es un derivado biosintético del ácido 7-aminocefalosporánico.

Cada jeringa desechable de 10 mL contiene 300 mg de cefapirina activa en un gel estable de aceite de cacahuete. Este producto fue fabricado mediante un proceso no esterilizador.

STORAGE AND HANDLING

Store at or below 25°C (77°F). Do not freeze. Avoid excessive heat.

Almacenar a una temperatura igual o inferior a 25°C (77°F). No congelar. Evitar el calor excesivo.

ACTION

In the non-lactating mammary gland, ToMORROW (cephapirin benzathine intramammary infusion) provides bactericidal levels of the active antibiotic, cephapirin, for a prolonged period of time. This prolonged activity is due to the low solubility of the cephapirin benzathine and to the slow release gel base.

Cephapirin is bactericidal to susceptible organisms; it is known to be highly active against Streptococcus agalactiae and Staphylococcus aureus including strains resistant to penicillin.

To determine the susceptibility of bacteria to cephapirin in the laboratory, the class disc, Cephalothin Susceptibility Test Discs, 30 mcg, should be used.

ACCIÓN

En la glándula mamaria no lactante, ToMORROW (infusión intramamaria de cefapirina benzatínica) proporciona niveles bactericidas del antibiótico activo, cefapirina, durante un período prolongado. Esta actividad prolongada se debe a la baja solubilidad de la cefapirina benzatínica y a la base de gel de liberación lenta. La cefapirina tiene una acción bactericida contra organismos susceptibles; se sabe que es extremadamente activa contra el Streptococcus agalactiae y el Staphylococcus aureus, incluyendo cepas resistentes a la penicilina. Para determinar en laboratorio la susceptibilidad de las bacterias a la cefapirina deberá utilizarse el disco de clase, Discos de Prueba de Susceptibilidad a la Cefalotina, 30 mcg.

INDICATIONS

For the treatment of mastitis in dairy cows during the dry period.

ToMORROW has been shown by extensive clinical studies to be efficacious in the treatment of mastitis in dry cows, when caused by Streptococcus agalactiae and Staphylococcus aureus including penicillin-resistant strains.

Treatment of the dry cow with ToMORROW is indicated in any cow known to harbor any of these organisms in the udder at drying off.

INDICACIONES

Para el tratamiento de mastitis bovina durante el período seco.

Extensos estudios clínicos han demostrado que ToMORROW es eficaz en el tratamiento de la mastitis en vacas secas, cuando esta es causada por el Streptococcus agalactiae y el Staphylococcus aureus, incluyendo cepas resistentes a la penicilina.

El tratamiento de la vaca seca con ToMORROW es recomendado para cualquier vaca que se sepa alberga cualquiera de estos organismos en la ubre en el momento del período de secado.

DOSAGE AND DIRECTIONS FOR USE

ToMORROW (cephapirin benzathine intramammary infusion) is for use in dry cows only. Infuse each quarter at the time of drying off with a single 10 mL syringe. Use no later than 30 days prior to calving.

Completely milk out all four quarters. The udder and teats should be thoroughly washed with warm water containing a suitable dairy antiseptic and dried, preferably using individual paper towels. Carefully scrub the teat end and orifice with 70% alcohol, using a separate swab for each teat. Allow to dry.

ToMORROW is packaged with the Opti-Sert® Protective Cap.

For partial insertion: Twist off upper portion of the Opti-Sert Protective Cap to expose 3–4 mm of the syringe tip.

For full insertion: Remove protective cap to expose the full length of the syringe tip.

Insert syringe tip into the teat canal and expel the entire contents of syringe into the quarter. Withdraw the syringe and gently massage the quarter to distribute the medication.

Do not infuse contents of the mastitis syringe into the teat canal if the Opti-Sert Protective Cap is broken or damaged.

DOSIS E INSTRUCCIONES DE USO

ToMORROW (infusión intramamaria de cefapirina benzatínica) debe usarse solamente en vacas secas. Introducir por infusión una sola jeringa de 10 ml en cada cuarto en el momento del secado. Administrar como máximo 30 días antes del parto.

Ordeñar por completo los cuatro cuartos. La ubre y los pezones deberán lavarse a fondo con agua tibia mezclada con un antiséptico adecuado para ganado lechero y secarse utilizando de preferencia toallas de papel individuales. Con cuidado frotar la punta del pezón y el orificio con una solución de alcohol al 70 %, empleando una torunda distinta para cada pezón. Dejar secar.

ToMORROW se envasa con el tapón protector Opti-Sert®.

Para una inserción parcial: Romper torciendo la parte superior del tapón protector Opti-Sert para dejar expuestos de 3 a 4 mm de la punta de la jeringa.

Para una inserción completa: Retirar el tapón protector para exponer completamente la punta de la jeringa.

Insertar la punta de la jeringa en el canal del pezón y expulsar todo el contenido de la jeringa dentro del cuarto. Retirar la jeringa y masajear suavemente el cuarto para distribuir el medicamento. No introducir por infusión el contenido de la jeringa para tratar la mastitis en el canal del pezón si el tapón protector Opti-Sert está roto o dañado.

PRECAUTIONS

ToMORROW should be administered with caution to subjects which have demonstrated some form of allergy, particularly to penicillin. Such reactions are rare; however, should they occur, consult your veterinarian.

PRECAUCIÓNS

ToMORROW debe administrarse con precaución a los animales que han presentado alguna forma de alergia, especialmente a la penicilina. Estas reacciones son raras; sin embargo, en caso de que ocurrieran, consulte al veterinario.

WITHDRAWAL PERIODS AND RESIDUE WARNINGS

1. For use in dry cows only.

2. Not to be used within 30 days of calving.

3. Milk from treated cows must not be used for food during the first 72 hours after calving.

4. Any animal infused with this product must not be slaughtered for food until 42 days after the latest infusion.

PERÍODOS DE RETIRO Y ADVERTENCIAS SOBRE RESIDUOS

1. Únicamente para uso en vacas secas.

2. No debe administrarse dentro del período de 30 días previos a la parición.

3. La leche extraída a vacas tratadas no debe utilizarse para consumo alimentario durante las primeras 72 horas después de la parición.

4. Cualquier animal al que se le haya aplicado la infusión de este producto no debe sacrificarse para consumo alimentario sino hasta que hayan transcurrido 42 días después de la última infusión.

CONTACT INFORMATION

For technical assistance or to report suspected adverse drug experiences, contact Boehringer Ingelheim Animal Health USA Inc. at 1-888-637-4251. For additional information about adverse drug experience reporting for animal drugs, contact FDA at 1-888-FDA-VETS or http://www.fda.gov/reportanimalae.

INFORMACIÓN DE CONTACTO

Para obtener asistencia técnica o para informar presuntas experiencias adversas con medicamentos, comuníquese con Boehringer Ingelheim Animal Health USA Inc. al 1-888-637-4251. Para obtener información adicional sobre la notificación de experiencias adversas con medicamentos para animales, comuníquese con la Administración de Alimentos y Medicamentos (Food and Drug Administration, FDA) al 1-888-FDA-VETS o en http://www.fda.gov/reportanimalae.

HOW SUPPLIED

ToMORROW (cephapirin benzathine intramammary infusion) is supplied in cartons containing 12 x 10 mL syringes with 12 convenient single use alcohol pads (NDC 0010-4755-01) and pails containing 144 x 10 mL syringes and 144 convenient single use alcohol pads (NDC 0010-4755-02).

FORMAS DE PRESENTACIÓN

ToMORROW (infusión intramamaria de cefapirina benzatínica) se suministra en cajas que contienen 12 jeringas de 10 ml con 12 útiles almohadillas con alcohol para un solo uso (NDC 0010-4755-01) y en contenedores que contienen 144 jeringas de 10 ml y 144 útiles almohadillas con alcohol para un solo uso (NDC 0010-4755-02).

© 2025 Boehringer Ingelheim Animal Health USA Inc. All rights reserved.

ToMORROW® is a registered trademark of Boehringer Ingelheim Animal Health USA Inc.

Opti-Sert is a registered trademark of Zoetis W LLC - used under license.

Origin China

Marketed by:
Boehringer Ingelheim Animal Health USA Inc.
Duluth, GA 30096

471801-03
Revised 07/2025
51759905

© 2025 Boehringer Ingelheim Animal Health USA Inc. Reservados todos los derechos.

ToMORROW® es una marca registrada de Boehringer Ingelheim Animal Health USA Inc.

Opti-Sert es una marca registrada de Zoetis W LLC - uso bajo licencia.

Origen: China

Comercializado por:
Boehringer Ingelheim Animal Health USA Inc.
Duluth, GA 30096

471801-03
Revised 07/2025
51759905